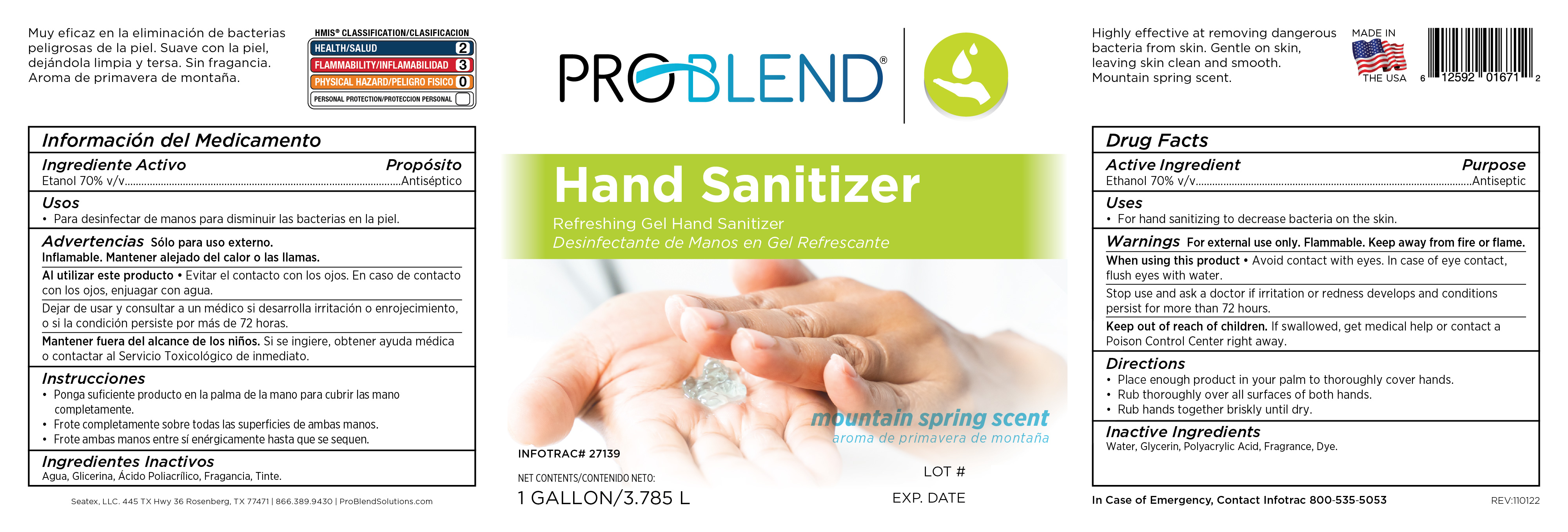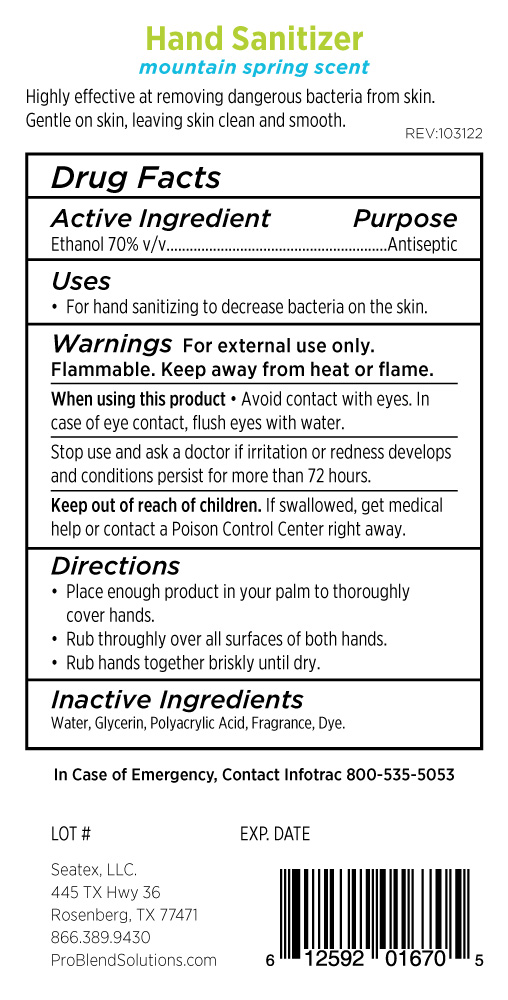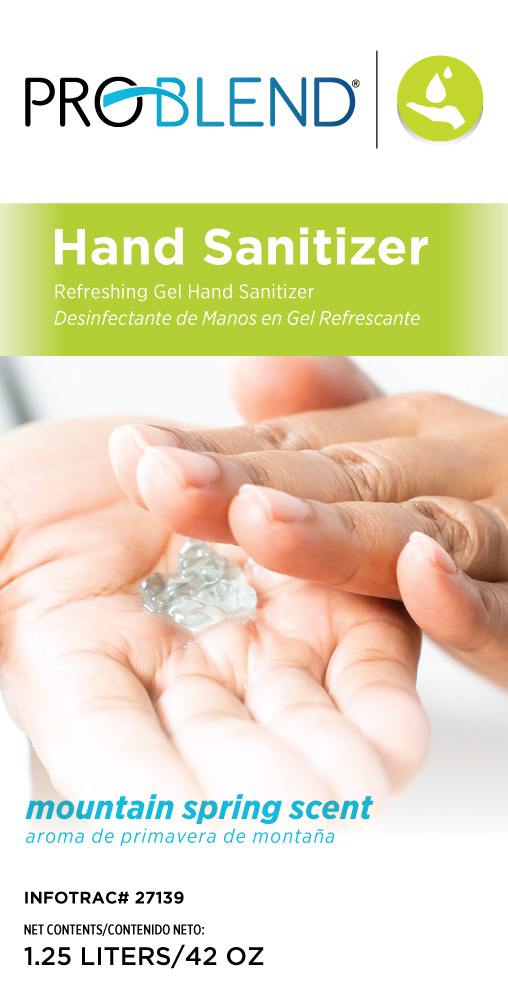 DRUG LABEL: Problend Hand Sanitizer Gel
NDC: 76250-140 | Form: GEL
Manufacturer: Seatex, LLC
Category: otc | Type: HUMAN OTC DRUG LABEL
Date: 20230126

ACTIVE INGREDIENTS: ALCOHOL 70 mL/70 mL
INACTIVE INGREDIENTS: METHACRYLIC ACID-ETHYL ACRYLATE COPOLYMER (1:1) TYPE A; FD&C BLUE NO. 1; GLYCERIN; WATER; FRAGRANCE CLEAN ORC0600327; FD&C YELLOW NO. 5

Formula 27139 Problend

Drug Facts

Active Ingredient Purpose

Ethanol 70% v/v....... Antiseptic

When using this product

Avoid contact with eyes. In case of eye contact, flush eyes with water.

Keep out of reach of children

If swallowed, get medical help or cantact a Poison Control Center right away.

Inactive Ingredients

Water, Glycerin, Polyacrylidc Acid, Fragrance, Dye.

Purpose Section

Antiseptic

Stop Use Section

Stop use and ask a doctor if irritation or redness develops and conditions persist for more than 72 hours.

Indications & Usage Section

Uses: For hand sanitizing to decrease bacteria on the skin.

Dosage and Administation Section

Directions

Place enough product in your palm to thoroughly cover hands. Rub thoroughly over all surfaces of both hands. Rub hands together briskly until dry.

Warnings

For external use only. Flammable. Keep away from fire or flame.